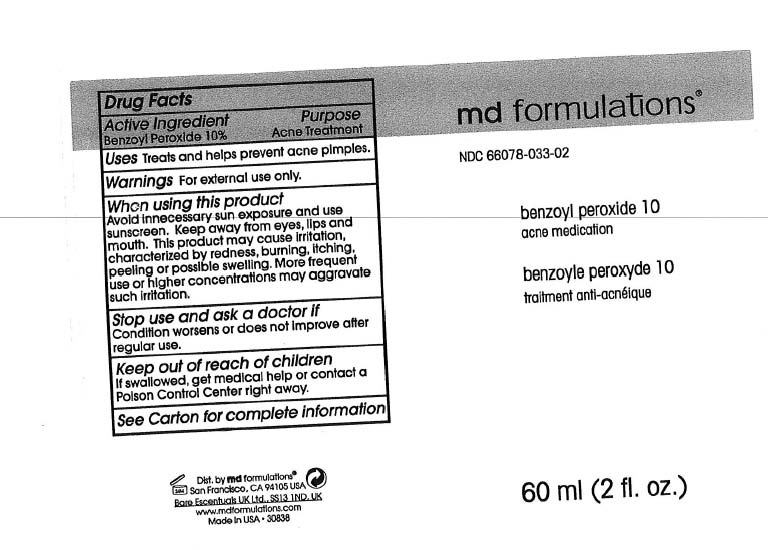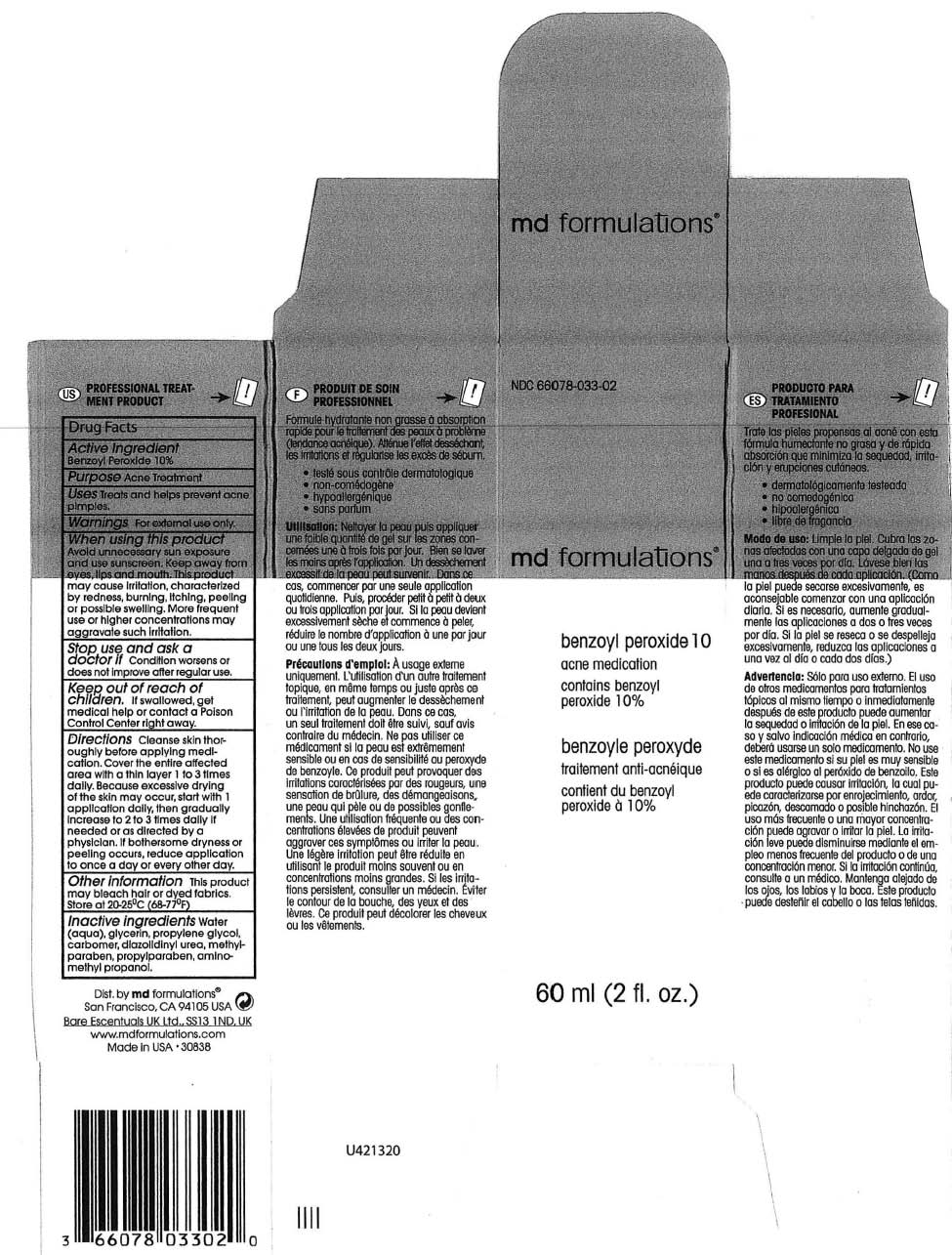 DRUG LABEL: Benzoyl Peroxide 
NDC: 66078-033 | Form: GEL
Manufacturer: MD Formulation
Category: otc | Type: HUMAN OTC DRUG LABEL
Date: 20110518

ACTIVE INGREDIENTS: BENZOYL PEROXIDE 10 g/100 g
INACTIVE INGREDIENTS: WATER; CARBOMER 934; PROPYLENE GLYCOL; DIAZOLIDINYL UREA; METHYLPARABEN; PROPYLPARABEN; AMINOMETHYLPROPANOL; GLYCERIN

Benzoyl Peroxide 10&%

ACTIVE INGREDIENT

Benzoyl Peroxide 10%

PURPOSE

Acne Treatment

INDICATIONS AND USAGE

Treats and helps prevent acne pimples.

WARNINGS

Foe external use only

KEEP OUT OF REACH OF CHILDREN

If swallowed, get medical help or contact a Poison Control Center right away.

DOSAGE AND ADMINISTRATION

Directions Cleanse skin thoroughly before applying medication. Cover the entire affected area with a thin layer 1 to 3 times dally. Because excessive drying of the skin may accur, start with 1 application daily, then gradually increase to 2 to 3 times daily If needed or as directed by a
physician. If bothersome dryness or peeling occurs, reduce application to once a day or every other other day.

Inactive Ingredients:
Water, glycerin, propylene glycol, carbomer, diazolidinyl urea, methylparaben, propylparaben, aminomethyl propanol.